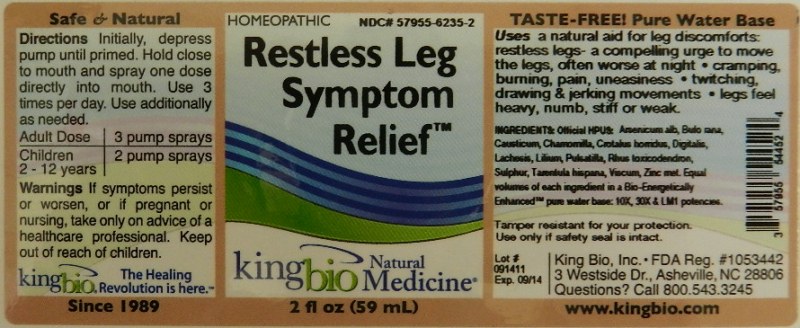 DRUG LABEL: Restless Leg Symptom Relief
NDC: 57955-6235 | Form: LIQUID
Manufacturer: King Bio Inc.
Category: homeopathic | Type: HUMAN OTC DRUG LABEL
Date: 20111220

ACTIVE INGREDIENTS: ARSENIC TRIOXIDE 10 [hp_X]/59 mL; BUFO BUFO CUTANEOUS GLAND 10 [hp_X]/59 mL; CAUSTICUM 10 [hp_X]/59 mL; MATRICARIA RECUTITA 10 [hp_X]/59 mL; CROTALUS HORRIDUS HORRIDUS VENOM 10 [hp_X]/59 mL; DIGITALIS 10 [hp_X]/59 mL; LACHESIS MUTA VENOM 10 [hp_X]/59 mL; LEDUM PALUSTRE TWIG 10 [hp_X]/59 mL; PULSATILLA VULGARIS 10 [hp_X]/59 mL; TOXICODENDRON PUBESCENS LEAF 10 [hp_X]/59 mL; SULFUR 10 [hp_X]/59 mL; LYCOSA TARANTULA 10 [hp_X]/59 mL; VISCUM ALBUM FRUIT 10 [hp_X]/59 mL; ZINC 10 [hp_X]/59 mL
INACTIVE INGREDIENTS: WATER

Restless Leg Symptom Relief

Active Ingredients

Official HPUS: Arsenicum Album, Bufo Rana, Causticum, Chamomilla, Crotalus Horridus, Digitalis Purpurea, Lachesis Mutus, Ledum Palustre, Pulsatilla, Rhus Toxicodendron, Sulphur, Tarentula Hispana, Viscum Album and Zincum Metallicum.

Reference Image restless leg.jpg

Inactive Ingredients

Bio-Energetically Enhanced pure water base 10X, 30X and LM1.

Reference image restless leg.jpg

Dosage and Administration

Directions: Initially depress pump until primed. Hold close to mouth and spray one dose directly into mouth. Use 3 times per day. Use additionally as needed.

Adult Dose: 3 pump sprays

Children: (2-12 years) 2 pump sprays

Reference image restless leg.jpg

Purpose

Use as a natural aid for leg discomforts: restless legs-a compelling urge to move the legs, often worse at night.

- cramping, burning, pain, uneasiness
- twitching, drawing and jerking movements
- legs feel heavy, numb, stiff or weak

Reference image restless leg.jpg

WARNINGS

If Symptoms persist or worsen, or if pregnant or nursing, take only on advice of a healthcare professional.

Tamper resistant for your protection, Use only if safety seal is intact.

Reference image restless leg.jpg

Keep out of reach of children.

Reference image restless leg.jpg

Indications and Usage

Use as a natural aid for leg discomforts: restless legs-a compelling urge to move the legs, often worse at night. Also use for cramping, burning, pain, uneasiness, twitching, drawing and jerking movements, legs feel heavy, numb, stiff or weak.

Reference image restless leg.jpg

PACKAGE LABEL

King Bio Inc.

3 Westside Drive

Asheville, NC 28806

Questions? Call 800.543.3245

www.kingbio.com